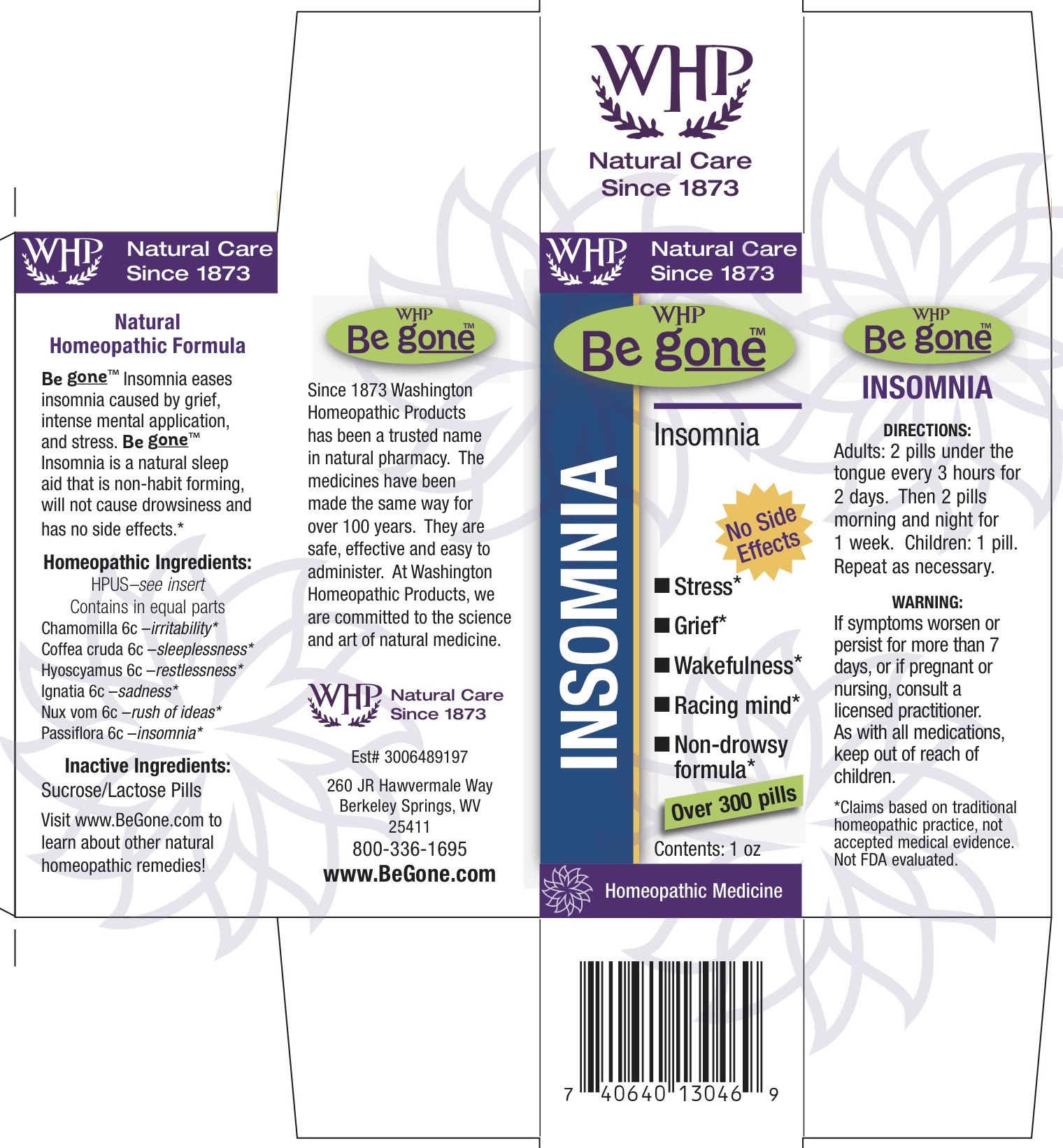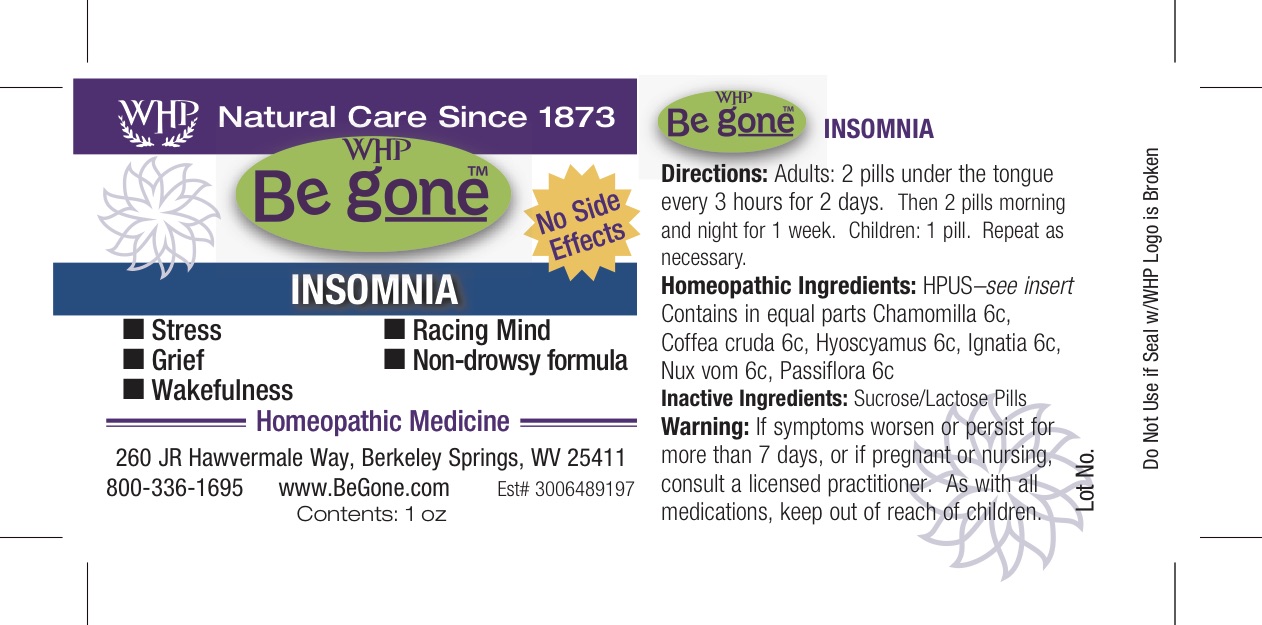 DRUG LABEL: Be gone Insomnia
NDC: 68428-726 | Form: PELLET
Manufacturer: Washington Homeopathic Products
Category: homeopathic | Type: HUMAN OTC DRUG LABEL
Date: 20181114

ACTIVE INGREDIENTS: MATRICARIA RECUTITA 6 [hp_C]/28 g; ARABICA COFFEE BEAN 6 [hp_C]/28 g; HYOSCYAMUS NIGER 6 [hp_C]/28 g; STRYCHNOS IGNATII SEED 6 [hp_C]/28 g; PASSIFLORA INCARNATA FLOWERING TOP 6 [hp_C]/28 g; STRYCHNOS NUX-VOMICA SEED 6 [hp_C]/28 g
INACTIVE INGREDIENTS: SUCROSE; LACTOSE

DRUG FACTS

ACTIVE INGREDIENTS

CHAMOMILLA 6C

COFFEA CRUDA 6C

HYOSCYAMUS 6C

IGNATIA 6C

NUX VOMICA 6C

PASSIFLORA 6C

USES

Eases insomnia caused by grief, intense mental application and stress. Is a natural sleep aid that is non-habit forming. Will not cause drowsiness and has no side effects.

KEEP OUT OF REACH OF CHILDREN

As with all medications, keep out of reach of children.

INDICATIONS

CHAMOMILLA Irritability

COFFEA CRUDA Sleeplessness

HYOSCYAMUS Twitching

IGNATIA Sadness

NUX VOMICA Vomiting

PASSIFLORA Insomnia

STOP USE AND ASK DOCTOR

If symptoms persist/worsen or if pregnant/nursing, stop use and consult your practitioner.

*Claims based on traditional homeopathic practice, not accepted medical evidence. Not FDA evaluated.

DIRECTIONS

Adults 2 pellets every 3 hours for 2 days. Then 2 pellets morning and night for 2 weeks.

Children: 1 pellet. Repeat as necessary.

INACTIVE INGREDIENTS

Sucrose/Lactose

PRINCIPAL DISPLAY PANEL

Be g oneTM Insomnia Label

Be g oneTM Insomnia Box